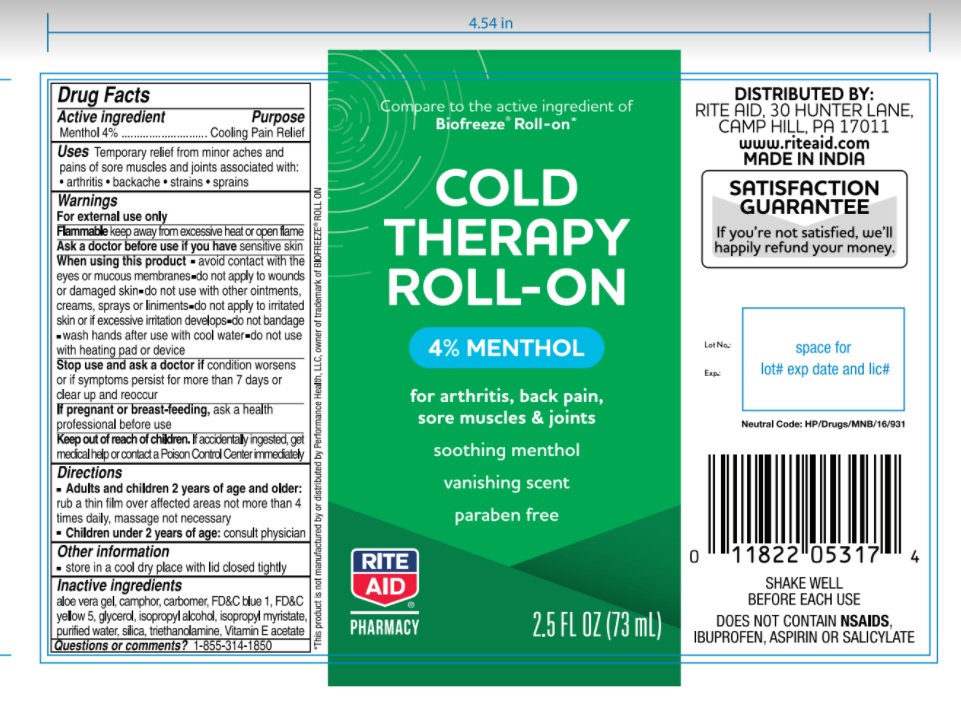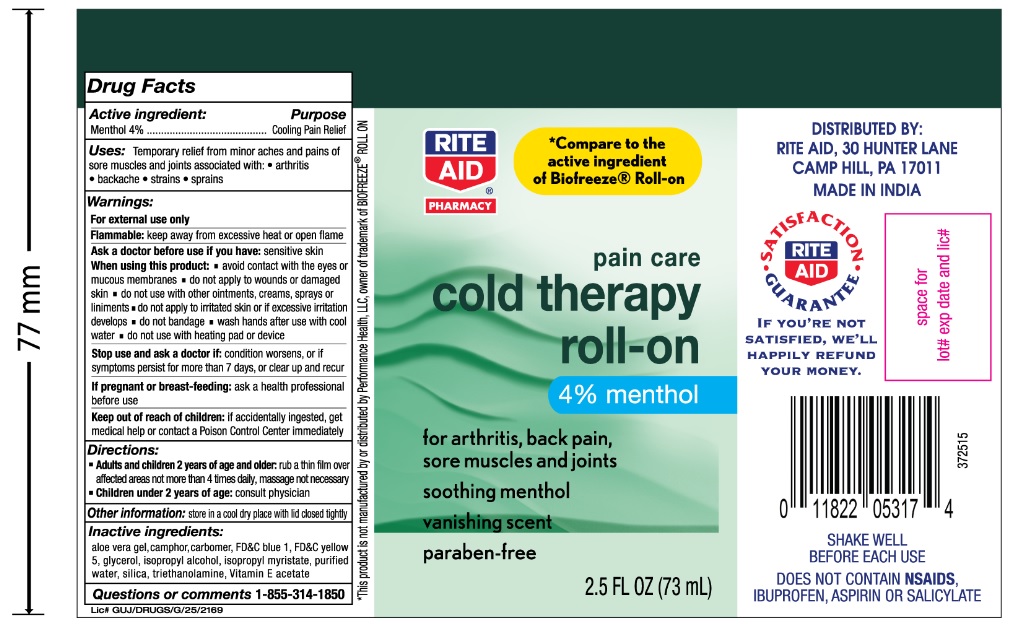 DRUG LABEL: Rite Aid Roll-On
NDC: 76168-313 | Form: GEL
Manufacturer: Velocity Pharma LLC
Category: otc | Type: HUMAN OTC DRUG LABEL
Date: 20201001

ACTIVE INGREDIENTS: MENTHOL 40 mg/1 mL
INACTIVE INGREDIENTS: SILICON DIOXIDE; .ALPHA.-TOCOPHEROL ACETATE; TROLAMINE; WATER; FD&C BLUE NO. 1; FD&C YELLOW NO. 5; ALOE VERA LEAF; ARNICA MONTANA FLOWER; FRANKINCENSE; CALENDULA OFFICINALIS FLOWER; GREEN TEA LEAF; GLYCERIN; ILEX PARAGUARIENSIS LEAF; ISOPROPYL ALCOHOL; ISOPROPYL MYRISTATE; MELISSA OFFICINALIS LEAF

Rite Aid Roll-On

Active Ingredients

Menthol USP 4%

Purpose

Cooling Pain Relief

Uses:

Temporary relief from minor aches and pains of sore muscles and joints associated with: - arthritis, - backache, - strains, - sprains

Warnings:

For external use only

Flammable:

Keep away from excessive heat or open flame

Ask a doctor before use if you have:

Sensitive skin

When using this product:

- Avoid contact with eyes or mucous membranes
- Do not apply to wounds or damaged skin.
- Do not use with other ointments, creams, sprays, or liniments.
- Do not apply to irritated skin or if excessive skin irritation develops.
- Do not bandage
- Wash hands after use with cool water
- Do not use with heating pad or device.

Stop use and ask a doctor if:

Condition worsens, or if symptoms persist for more than 7 days, or clear up and reoccur

If pregnant or breast-feeding:

Ask a health professional before use

Keep out of reach of children:

If accidentally ingested, get medical help or contact a Poison Control Center immediately.

Directions

Adults and children 2 years of age and older: Rub a thin film over affected areas not more than 4 times daily; massage not necessary
Children under 2 years of age: Consult physician

Inactive Ingredients:

Aloe Vera gel, Camphor, Carbomer, FD&C blue 1, FD&C yellow 5 Glycerol, Isopropyl Alcohol, Ispropyl Myristate, Purified water, Silica, triethanolamine, Tocopheryl (Vitamin E) Acetate,

Other Information:

Store in a cool dry place with lid closed tightly

Questions or Comments

1-855-314-1850